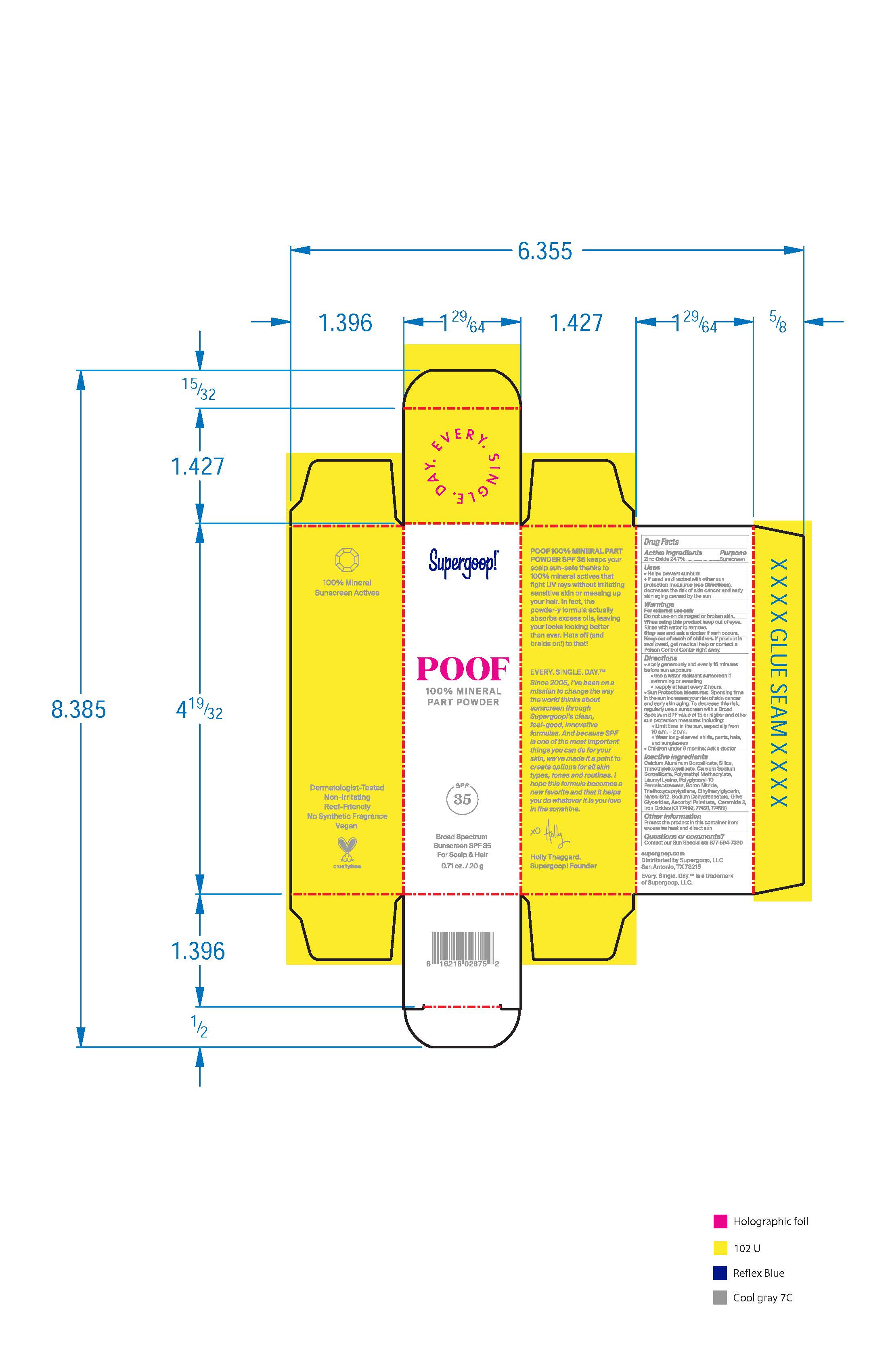 DRUG LABEL: Poof 100% Mineral Part Powder SPF 35
NDC: 75936-214 | Form: POWDER
Manufacturer: Supergoop, LLC
Category: otc | Type: HUMAN OTC DRUG LABEL
Date: 20241204

ACTIVE INGREDIENTS: ZINC OXIDE 24.7 g/100 g
INACTIVE INGREDIENTS: SODIUM DEHYDROACETATE; FERRIC OXIDE RED; FERROSOFERRIC OXIDE; CALCIUM ALUMINUM BOROSILICATE; SILICON DIOXIDE; ETHYLHEXYLGLYCERIN; TRIMETHYLSILOXYSILICATE (M/Q 0.6-0.8); POLYGLYCERYL-10 PENTASTEARATE; LAUROYL LYSINE; POLY(METHYL METHACRYLATE; 450000 MW); ASCORBYL PALMITATE; CERAMIDE NP; FERRIC OXIDE YELLOW; BORON NITRIDE; TRIETHOXYCAPRYLYLSILANE

Poof 100% Mineral Part Powder SPF 35

Active Ingredients Purpose

Zinc Oxide 24.7 Sunscreen

Uses

- Helps Prevent Sunburn
- If used as directed with other sun protection measures (see Directions), decreases the risk of skin cancer and early skin aging caused by the sun

Keep out of reach of children. If product is swallowed, get medical help or contact a poison Control Center right away

Stop use and ask a doctor if rash occurs

Warnings

For external use only

Do not use on damaged or broken skin

When using this product keep out of eyes. Rinse with water to remove.

Directions

- apply generously and evenly 15 minutes before sun exposure
- use a water resistant sunscreen if swimming or sweating
- reapply at least every 2 hours.
- Sun Protection Measures Spending time in the sun increases your risk of

skin cancer and early skin aging. To decrease this risk, regularly use a
sunscreen with a Broad-Spectrum SPF value of 15 or higher and other sun
protection measures including:

• limit your time in the sun, especially from 10 a.m. – 2 p.m.

• wear long-sleeved shirts, pants, hats, and sunglasses

• Children under 6 months of age: ask a doctor.

Inactive ingredients

Calcium Aluminum Borosilicate, Silica, Trimethylsiloxysiloxysilicate, Calcium Sodium Borosilicate, Polymethyl Methacryate, Lauroyl Lysine, Polyglyceryl-10 Pentaisostearate, Boron Nitride, Triethoxycaprylysilane, Ethylhexylglycerin, Nylon-6/12, Sodium Dehydroacetate, Olive Glycerides, Ascorbyl Palmitate, Ceramide 3, Iron Oxides (CI 77492, 77491, 77499)

PACKAGE LABEL

Supergoop!
Poof
100% Mineral powder
SPF 35
Broad Spectrum
Sunscreen SPF 35
For Scalp and Hair
0.71 oz. / 20 g